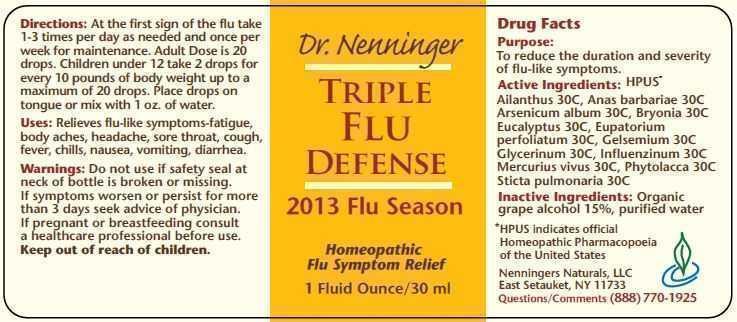 DRUG LABEL: Triple Flu Defense
                
NDC: 42731-012 | Form: LIQUID
Manufacturer: Nenningers Naturals, LLC
Category: homeopathic | Type: HUMAN OTC DRUG LABEL
Date: 20130228

ACTIVE INGREDIENTS: AILANTHUS ALTISSIMA FLOWERING TWIG 30 [hp_C]/30 mL; CAIRINA MOSCHATA HEART/LIVER AUTOLYSATE 30 [hp_C]/30 mL; ARSENIC TRIOXIDE 30 [hp_C]/30 mL; BRYONIA ALBA ROOT 30 [hp_C]/30 mL; EUCALYPTUS GLOBULUS LEAF 30 [hp_C]/30 mL; EUPATORIUM PERFOLIATUM FLOWERING TOP 30 [hp_C]/30 mL; GELSEMIUM SEMPERVIRENS ROOT 30 [hp_C]/30 mL; GLYCERIN 30 [hp_C]/30 mL; INFLUENZA A VIRUS A/NEW CALEDONIA/20/99 (H1N1) ANTIGEN (PROPIOLACTONE INACTIVATED) 30 [hp_C]/30 mL; INFLUENZA B VIRUS B/HONG KONG/330/2001 ANTIGEN (PROPIOLACTONE INACTIVATED) 30 [hp_C]/30 mL; MERCURY 30 [hp_C]/30 mL; PHYTOLACCA AMERICANA ROOT 30 [hp_C]/30 mL; LOBARIA PULMONARIA 30 [hp_C]/30 mL; INFLUENZA A VIRUS A/PANAMA/2007/99 (H3N2) ANTIGEN (PROPIOLACTONE INACTIVATED) 30 [hp_C]/30 mL
INACTIVE INGREDIENTS: ALCOHOL; WATER

Active ingredients: HPUS*

Ailanthus 30C, Anas barbariae 30C

Arsenicum album 30C, Bryonia 30C

Eucalyptus 30C, Eupatorium

perfoliatum 30C, Gelsemium 30C

Glycerinum 30C, Influenzinum 30C

Mercurius vivus 30C, Phytolacca 30C

Sticta pulmonaria 30C

Inactive Ingredients: Organic

grape alcohol 15%, purified water

Purpose:

To reduce the duration and severity

of flu-like symptoms.

INDICATIONS AND USAGE

Uses: Relieves flu-like symptoms - fatigue, body aches, headache, sore throat, cough, fever, chills, nausea, vomiting, diarrhea.

DOSAGE AND ADMINISTRATION

Directions: At the first sign of the flu take 1-3 times per day as needed and oncer per week for maintenance. Adult Dose is 20 drops. Children under 12 take 2 drops for every 10 pounds of body weight up to a maximum of 20 drops. Place drops on tongue or mix with 1 oz. water.

WARNINGS

Warnings: Do not use if safety seal at neck of bottle is broken or missing.

ASK DOCTOR

If symptoms worsen or persist for more than 3 days seek advice of physician. If pregnant or breastfeeding consult a healthcare professional before use.

Keep out of reach of children.

QUESTIONS

Nenningers Naturals, LLC

East Setauket, NY 11733

Questions/Comments (888) 770-1925

DESCRIPTION

*HPUS indicates official Homeopathic Pharmacopeia of the United States

PACKAGE LABEL

Dr. Nenninger

TRIPLE

FLU

DEFENSE

2013 Flu Season

Homeopathic

Flu Symptom Relief

1 Fluid Ounce/30 ml